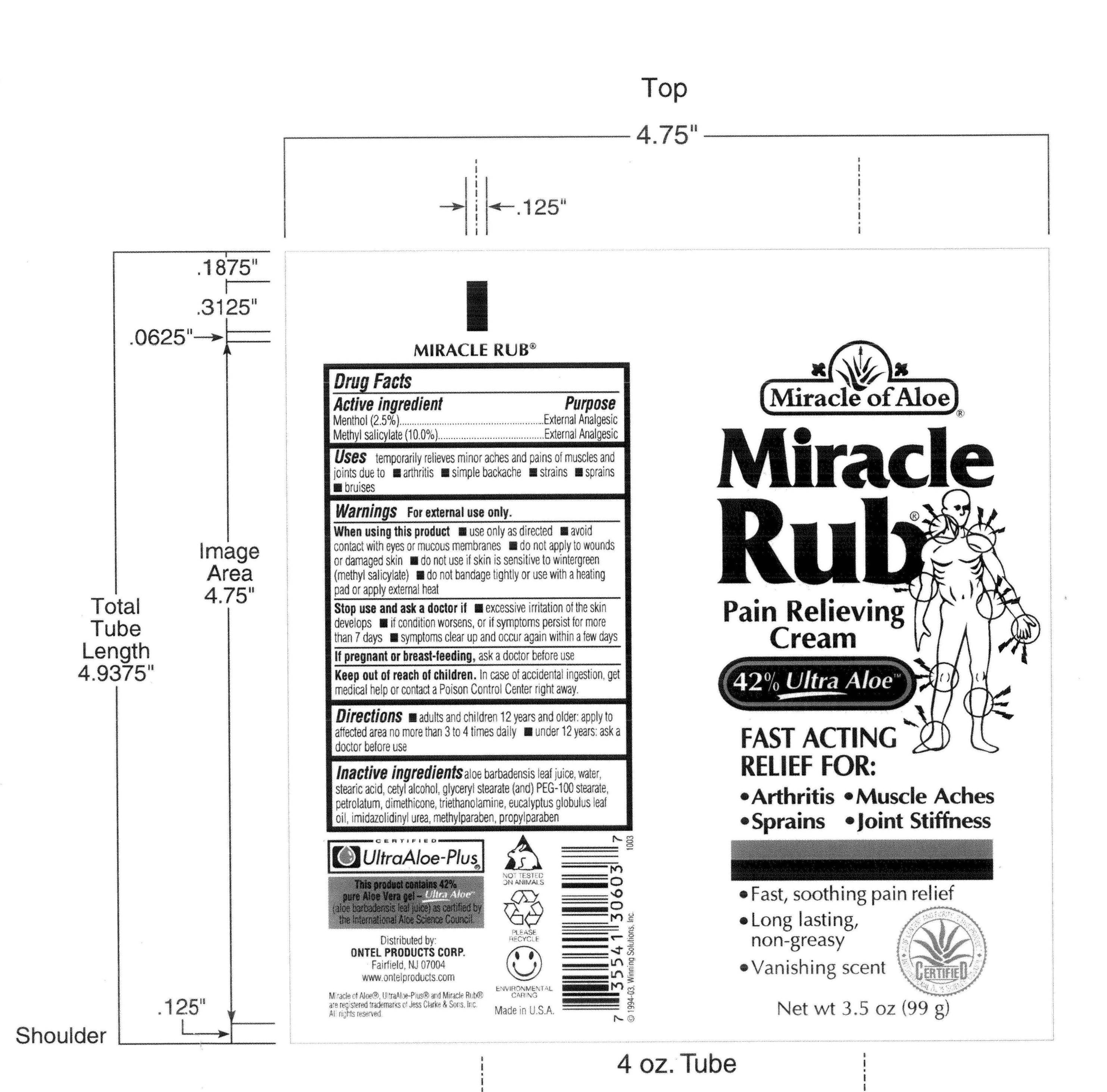 DRUG LABEL: Miracle Rub
NDC: 66391-0603 | Form: CREAM
Manufacturer: Winning Solutions
Category: otc | Type: HUMAN OTC DRUG LABEL
Date: 20110405

ACTIVE INGREDIENTS: MENTHOL 2.475 g/99 g; METHYL SALICYLATE 9.9 g/99 g
INACTIVE INGREDIENTS: WATER; STEARIC ACID; GLYCERYL MONOSTEARATE; PEG-100 STEARATE; Dimethicone; METHYLPARABEN; Propylparaben

Active Ingredient : Menthol , Methyl Salicylate

Purpose : External Analgesic

Warnings : For external use only

Keep Out of Reach of Children : In case of accidental ingestion , get medical help or contact a Position Control center right away.

DOSAGE AND ADMINISTRATION

Directions : adults and children 12 years and older ; apply to affected area no more than 3 to 4 times daily
under 12 years: ask a doctor before use

INACTIVE INGREDIENT

Inactive Ingredients : aloe barbadensis leaf juice , water , stearic acid , cetyl alcohol , glyceryl stearate (and) PEG-100 stearate , petrolatum , dimethicone, triethanolamine , eucalyptus globulus leaf oil , imidazolidinyl urea, methylparaben , propylparaben

INDICATIONS AND USAGE

Uses : Temporarily relieves minor aches and pains of muscles and joints due to * arthritis * simple backache * strains * sprains * bruises